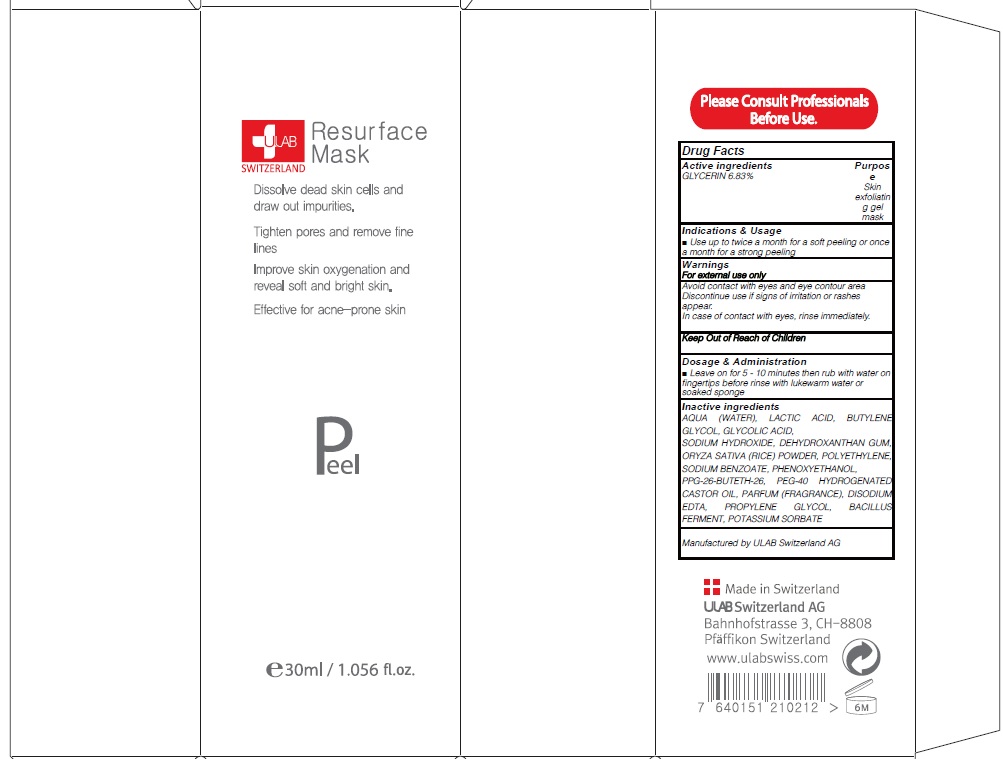 DRUG LABEL: RESURFACE MASK
NDC: 71276-150 | Form: CREAM
Manufacturer: ULAB
Category: otc | Type: HUMAN OTC DRUG LABEL
Date: 20170322

ACTIVE INGREDIENTS: GLYCERIN 2.04 g/30 mL
INACTIVE INGREDIENTS: WATER; LACTIC ACID

ACTIVE INGREDIENT

Active ingredients: GLYCERIN 6.83%

INACTIVE INGREDIENT

Inactive ingredients: AQUA (WATER), LACTIC ACID, BUTYLENE GLYCOL, GLYCOLIC ACID, SODIUM HYDROXIDE, DEHYDROXANTHAN GUM, ORYZA SATIVA (RICE) POWDER, POLYETHYLENE, SODIUM BENZOATE, PHENOXYETHANOL, PPG-26-BUTETH-26, PEG-40 HYDROGENATED CASTOR OIL, PARFUM (FRAGRANCE), DISODIUM EDTA, PROPYLENE GLYCOL, BACILLUS FERMENT, POTASSIUM SORBATE

PURPOSE

Purpose: Skin exfoliating gel mask

WARNINGS

Warnings: For external use only Avoid contact with eyes and eye contour area Discontinue use if signs of irritation or rashes appear. In case of contact with eyes, rinse immediately.

KEEP OUT OF REACH OF CHILDREN

INDICATIONS & USAGE

Indications & Usage: Use up to twice a month for a soft peeling or once a month for a strong peeling

DOSAGE & ADMINISTRATION

Dosage & Administration: Leave on for 5 - 10 minutes then rub with water on fingertips before rinse with lukewarm water or soaked sponge